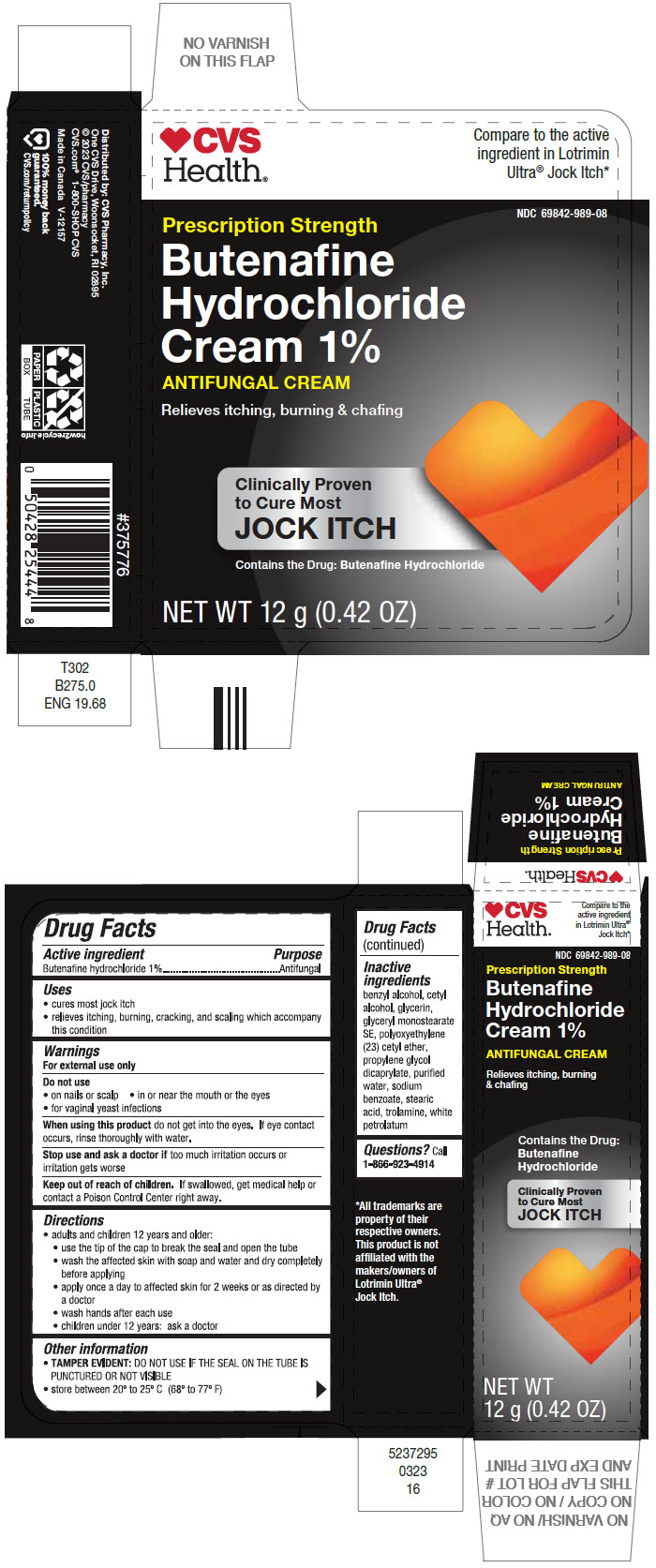 DRUG LABEL: Butenafine Hydrochloride 1%
NDC: 69842-989 | Form: CREAM
Manufacturer: CVS Pharmacy
Category: otc | Type: HUMAN OTC DRUG LABEL
Date: 20250703

ACTIVE INGREDIENTS: BUTENAFINE HYDROCHLORIDE 10 mg/1 g
INACTIVE INGREDIENTS: BENZYL ALCOHOL; CETYL ALCOHOL; GLYCERIN; GLYCERYL STEARATE SE; CETETH-23; PROPYLENE GLYCOL DICAPRYLATE; WATER; SODIUM BENZOATE; STEARIC ACID; TROLAMINE; PETROLATUM

Butenafine Hydrochloride Cream 1%

Drug Facts

Active ingredient

Butenafine hydrochloride 1%

Purpose

Antifungal

Uses

- cures most jock itch
- relieves itching, burning, cracking, and scaling which accompany this condition

Warnings

For external use only

Do not use

- on nails or scalp
- in or near the mouth or the eyes
- for vaginal yeast infections

WHEN USING

When using this productdo not get into the eyes. If eye contact occurs, rinse thoroughly with water.

Stop use and ask a doctor iftoo much irritation occurs or irritation gets worse

Keep out of reach of children.If swallowed, get medical help or contact a Poison Control Center right away.

Directions

- adults and children 12 years and older:
  - use the tip of the cap to break the seal and open the tube
  - wash the affected skin with soap and water and dry completely before applying
  - apply once a day to affected skin for 2 weeks or as directed by a doctor
  - wash hands after each use
  - children under 12 years: ask a doctor

Other information

- TAMPER EVIDENT:DO NOT USE IF THE SEAL ON THE TUBE IS PUNCTURED OR NOT VISIBLE
- store between 20º to 25º C (68º to 77º F)

Inactive ingredients

benzyl alcohol, cetyl alcohol, glycerin, glyceryl monostearate SE, polyoxyethylene (23) cetyl ether, propylene glycol dicaprylate, purified water, sodium benzoate, stearic acid, trolamine, white petrolatum

Questions?

Call 1-866-923-4914

Distributed by: CVS Pharmacy, Inc.
One CVS Drive, Woonsocket, RI 02895

PRINCIPAL DISPLAY PANEL - 12 g Tube Carton

CVS
Health®

Compare to the active
ingredient in Lotrimin
Ultra®Jock Itch*

NDC 69842-989-08

Prescription Strength
Butenafine
Hydrochloride
Cream 1%
ANTIFUNGAL CREAM

Relieves itching, burning & chafing

Clinically Proven
to Cure Most
JOCK ITCH

Contains the Drug: Butenafine Hydrochloride

NET WT 12 g (0.42 OZ)